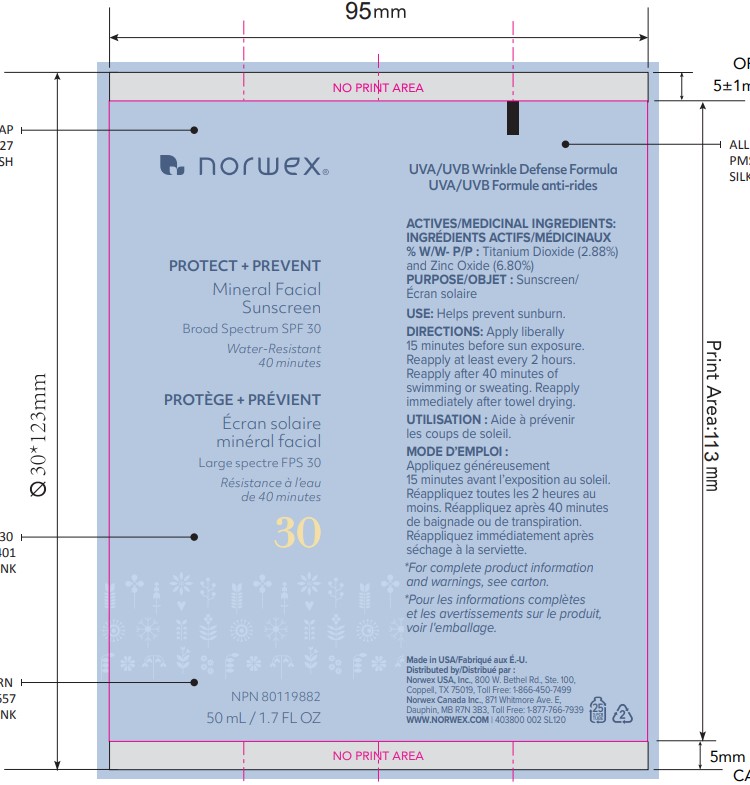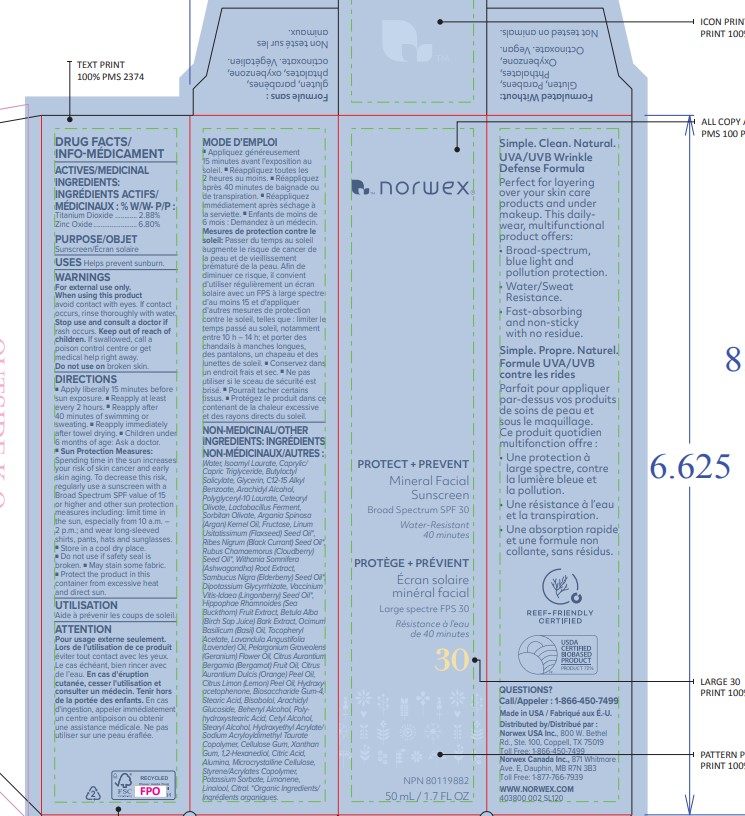 DRUG LABEL: NORWEX Protect Prevent Mineral Facial Sunscreen Broad Spectrum SPF30
NDC: 68577-158 | Form: LOTION
Manufacturer: COSMAX USA, CORPORATION
Category: otc | Type: HUMAN OTC DRUG LABEL
Date: 20241226

ACTIVE INGREDIENTS: TITANIUM DIOXIDE 2.88 mg/100 mg; ZINC OXIDE 6.8 mg/100 mg
INACTIVE INGREDIENTS: POLYHYDROXYSTEARIC ACID (2300 MW); DOCOSANOL; CETYL ALCOHOL; HYDROXYETHYL ACRYLATE/SODIUM ACRYLOYLDIMETHYL TAURATE COPOLYMER (45000 MPA.S AT 1%); 1,2-HEXANEDIOL; ALUMINUM OXIDE; LEMON OIL; LIMONENE, (+/-)-; LINALOOL, (+/-)-; CITRAL; ORANGE OIL; MEDIUM-CHAIN TRIGLYCERIDES; HYDROXYPHENYL PROPAMIDOBENZOIC ACID; WATER; ISOAMYL LAURATE; BUTYLOCTYL SALICYLATE; GLYCERIN; ALKYL (C12-15) BENZOATE; ARACHIDYL ALCOHOL; POLYGLYCERYL-10 LAURATE; CETEARYL OLIVATE; LIMOSILACTOBACILLUS FERMENTUM; SORBITAN OLIVATE; ARGANIA SPINOSA SEED; FRUCTOSE; LINSEED OIL; RIBES NIGRUM SEED OIL; SAMBUCUS NIGRA SEED OIL; GLYCYRRHIZINATE DIPOTASSIUM; RUBUS CHAMAEMORUS SEED OIL; LINGONBERRY SEED OIL; HIPPOPHAE RHAMNOIDES FRUIT; BETULA PUBESCENS BARK; BASIL OIL; .ALPHA.-TOCOPHEROL ACETATE; LAVENDER OIL; PELARGONIUM GRAVEOLENS FLOWER OIL; POTASSIUM SORBATE; BIOSACCHARIDE GUM-4; STEARIC ACID; XANTHAN GUM; CELLULOSE, MICROCRYSTALLINE; BERGAMOT OIL; HYDROXYACETOPHENONE; LEVOMENOL; ARACHIDYL GLUCOSIDE; STEARYL ALCOHOL; CARBOXYMETHYLCELLULOSE SODIUM, UNSPECIFIED; ANHYDROUS CITRIC ACID

NORWEX Protect + Prevent Mineral Facial Sunscreen Broad Spectrum SPF30

Active Ingredients

ZInc Oxide 6.8%

Titanum Dioxide 2.88%

Purpose

Sunscreen

USES

- helps prevent sunburn

Warnings

For extenal use only

When using this product keep out of eyes. Rinse with water to remove.

Stop use and ask a doctor ifrash occurs

Keep out of reach of children.If swallowed, get medical help or contact a Poison Control Center right away.

Do not use on broken skin

DIRECTIONS

- apply generously 15 minutes before sun exposure
- reapply at least every 2 hours
- Reapply after 40 minutes of swimming or sweating
- Reapply immediately after towel drying.
- children under 6 months of age:Ask a doctor
- Sun Protection Measures.Spending time in the sun

increases your risk of skin cancer and early skin aging. To decrease

this risk, regularly use a sunscreen with a Broad Spectrum SPF

value of 15 or higher and other sun protection measures including:

- limit time in the sun, especially from 10 a.m. - 2 p.m.
- wear long-sleeved shirts, pants, hats, and sunglasses
- Store in a cool dry place
- Do not use if safety seal is broken
- May stain some fabric.
- Protect the product in this container from excessive heat and direct sun.

Inactive ingredients:

Water, Isoamyl Laurate, Caprylic/ Capric Triglyceride, Butyloctyl Salicylate, Glycerin, C12-15 Alkyl Benzoate, Arachidyl Alcohol, Polyglyceryl-10 Laurate, Cetearyl Olivate, Lactobacillus Ferment, Sorbitan Olivate, Argania Spinosa (Argan) Kernel Oil, Fructose, Linum Usitatissimum (Flaxseed) Seed Oil*, Ribes Nigrum (Black Currant) Seed Oil*, Rubus Chamaemorus (Cloudberry) Seed Oil*, Withania Somnifera (Ashwagandha) Root Extract, Sambucus Nigra (Elderberry) Seed Oil*, Dipotassium Glycyrrhizate, Vaccinium Vitis-Idaea (Lingonberry) Seed Oil*, Hippophae Rhamnoides (Sea Buckthorn) Fruit Extract, Betula Alba (Birch Sap Juice) Bark Extract, Ocimum Basilicum (Basil) Oil, Tocopheryl Acetate, Lavandula Angustifolia (Lavender) Oil, Pelargonium Graveolens (Geranium) Flower Oil, Citrus Aurantium Bergamia (Bergamot) Fruit Oil, Citrus Aurantium Dulcis (Orange) Peel Oil, Citrus Limon (Lemon) Peel Oil, Hydroxy[1]acetophenone, Biosaccharide Gum-4, Stearic Acid, Bisabolol, Arachidyl Glucoside, Behenyl Alcohol, Poly[1]hydroxystearic Acid, Cetyl Alcohol, Stearyl Alcohol, Hydroxyethyl Acrylate/ Sodium Acryloyldimethyl Taurate Copolymer, Cellulose Gum, Xanthan Gum, 1,2-Hexanediol, Citric Acid, Alumina, Microcrystalline Cellulose, Styrene/Acrylates Copolymer, Potassium Sorbate, Limonene, Linalool, Citral.

OTHER INFORMATION

- Protect the product in this container from excessive heat and direct sun

QUESTIONS or COMMENTS

visit www.glossier.com or call toll-free
1-844-OK-GTEAM 1-844-654-8326

PRIMARY PACKAGE

Secondary Package